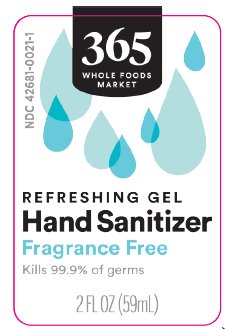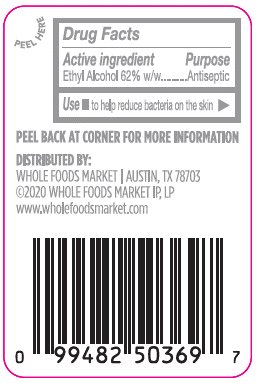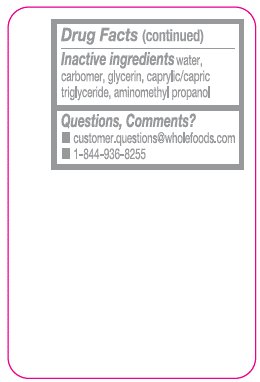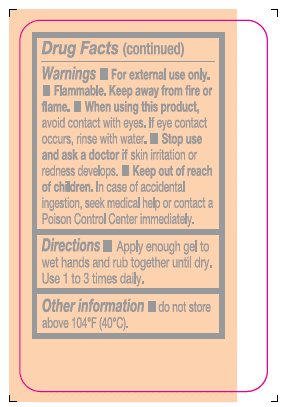 DRUG LABEL: Refreshing Gel Hand Sanitizer
NDC: 42681-0021 | Form: GEL
Manufacturer: Whole Foods Market
Category: otc | Type: HUMAN OTC DRUG LABEL
Date: 20200626

ACTIVE INGREDIENTS: ALCOHOL 69 mg/100 mL
INACTIVE INGREDIENTS: WATER; CARBOMER HOMOPOLYMER, UNSPECIFIED TYPE; GLYCERIN; MEDIUM-CHAIN TRIGLYCERIDES; AMINOMETHYLPROPANOL

Drug Facts

Active ingredient

Ethyl Alcohol 62% w/w

Purpose

Antiseptic

Use

to help reduce bacteria on the skin

Warnings

- For external use only.
- Flammable. Keep away from fire or flame.
- When using this product, avoid contact with eyes. If eye contact occurs, rinse with water.
- Stop use and ask a doctor if skin irritation or redness develops.

Keep Out of Reach of Children

In case of accidental ingestion, seek medical help or contact a Poison Control Center immediately.

Directions

Apply enough gel to wet hands and rub together until dry. Use 1 to 3 times daily.

Other information

do not store above 104°F (40°C).

Inactive Ingredients

water, carbomer, glycerin, caprylic/capric triglyceride, aminomethyl propanol

DISTRIBUTED BY:

WHOLE FOODS MARKET

AUSTIN, TX 78703

©2020 WHOLE FOODS MARKET IP, LP

www.wholefoodsmarket.com
Questions, Comments?

- customer.questions@wholefoods.com
- 1-844-936-8255